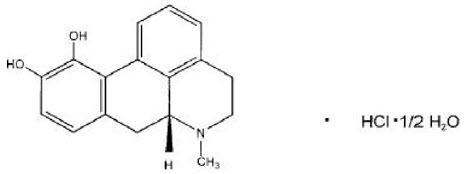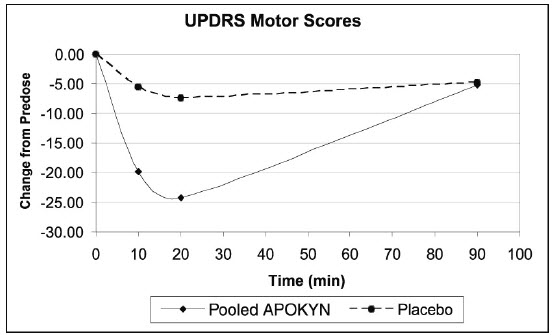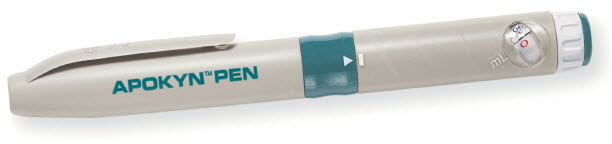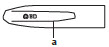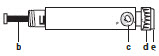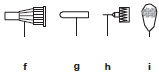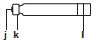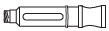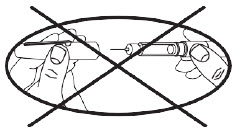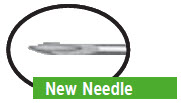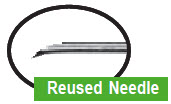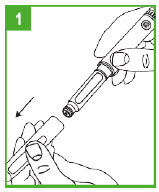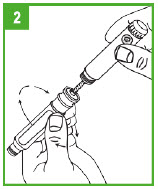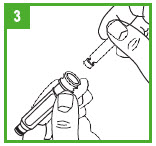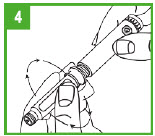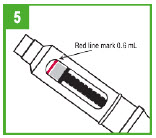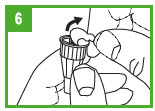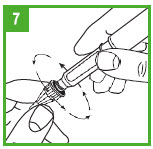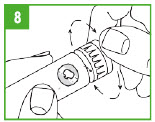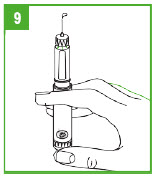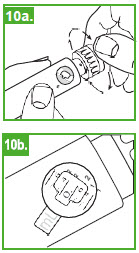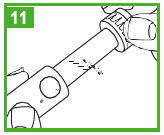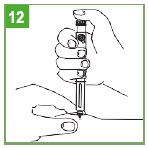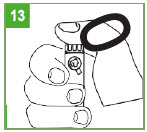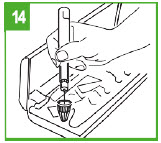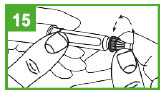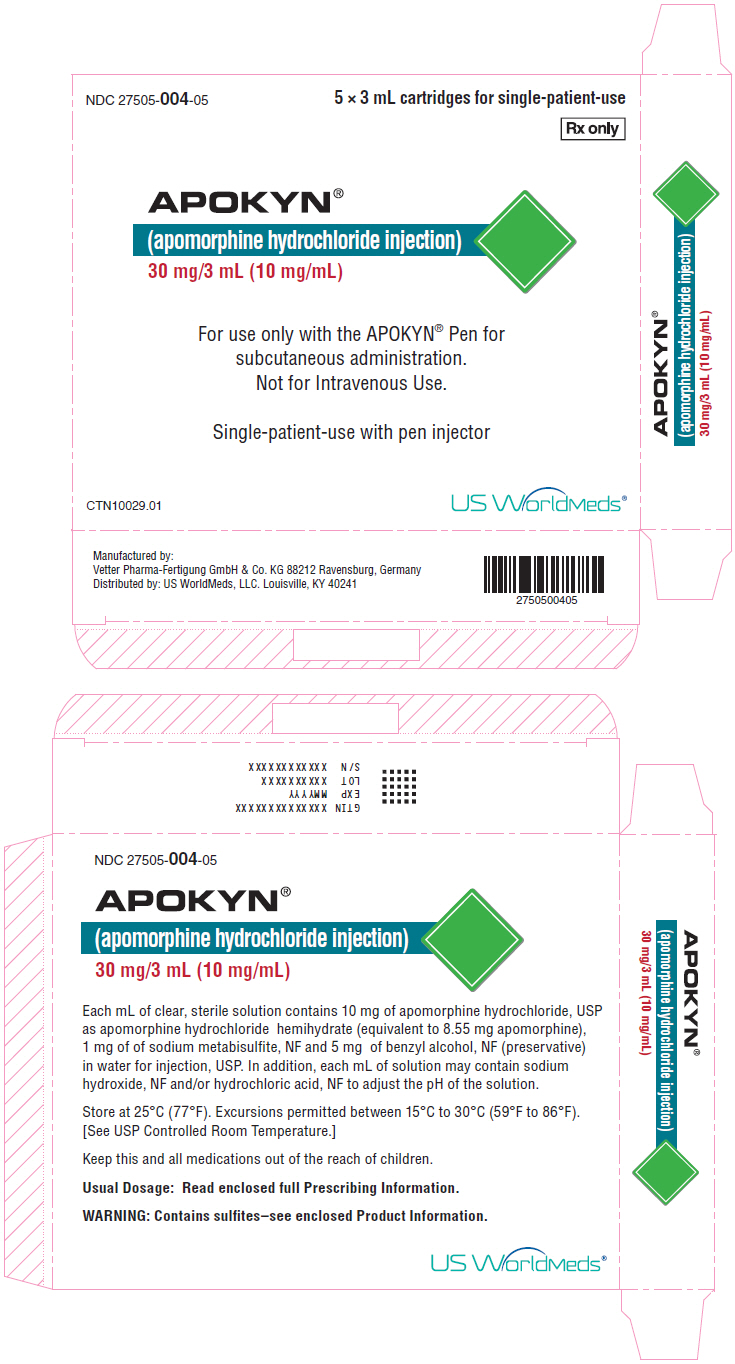 DRUG LABEL: APOKYN
NDC: 27505-004 | Form: INJECTION
Manufacturer: MDD US Operations, LLC
Category: prescription | Type: HUMAN PRESCRIPTION DRUG LABEL
Date: 20241010

ACTIVE INGREDIENTS: APOMORPHINE HYDROCHLORIDE 30 mg/3 mL
INACTIVE INGREDIENTS: SODIUM METABISULFITE 3 mg/3 mL; BENZYL ALCOHOL 15 mg/3 mL; WATER; SODIUM HYDROXIDE; HYDROCHLORIC ACID

HIGHLIGHTS OF PRESCRIBING INFORMATION

APOKYN ® - These highlights do not include all the information needed to use APOKYN® safely and effectively. See full prescribing information for APOKYN®.
APOKYN® (apomorphine hydrochloride injection), for subcutaneous use
Initial U.S. Approval: 2004

RECENT MAJOR CHANGES

Dosage and Administration (2.2, 2.3) | 06/2022
Warnings and Precautions, Hemolytic Anemia (5.8) | 05/2022

1 INDICATIONS AND USAGE

APOKYN is a non-ergoline dopamine agonist indicated for the acute, intermittent treatment of hypomobility, "off" episodes ("end-of-dose wearing off" and unpredictable "on/off" episodes) associated with advanced Parkinson's disease (1)

2 DOSAGE AND ADMINISTRATION

- For subcutaneous use only (2.1)
- Always express APOKYN dose in mL to minimize dosing errors (2.1)
- The starting dose of APOKYN is 0.1 mL (1mg) to 0.2 mL (2 mg); give the first dose under medical supervision; titrate the dose to effect and tolerance; the maximum recommended dose is 0.6 mL (6 mg) (2.3)
- Treatment with trimethobenzamide is recommended, starting 3 days prior to the first dose of APOKYN. Treatment with trimethobenzamide should only be continued as long as necessary to control nausea and vomiting, and generally no longer than two months (2.2, 5.2, 6.1, 17)
- APOKYN doses must be separated by at least 2 hours (2.5)
- Renal impairment: reduce test dose, and reduce starting dose to 0.1 mL (1 mg) (2.4, 8.6, 12.3)

3 DOSAGE FORMS AND STRENGTHS

Injection; 30 mg/3 mL (10 mg/mL) as a clear, colorless, sterile solution available in single-patient-use cartridges (3, 16)

4 CONTRAINDICATIONS

- Concomitant use of APOKYN with 5HT3 antagonists, including antiemetics (e.g., ondansetron, granisetron, dolasetron, palonosetron) and alosetron, is contraindicated (4)
- Hypersensitivity to apomorphine, its excipients or sodium metabisulfite (4, 5.13)

5 WARNINGS AND PRECAUTIONS

- For subcutaneous use only; thrombus formation and pulmonary embolism have followed intravenous administration of APOKYN (5.1)
- Falling asleep during activities of daily living, and daytime somnolence may occur (5.3)
- Syncope and hypotension/orthostatic hypotension may occur (5.4)
- Falls may occur, or increase (5.5)
- May cause hallucinations and psychotic-like behavior (5.6)
- May cause dyskinesia or exacerbate pre-existing dyskinesia (5.7)
- May cause hemolytic anemia (5.8)
- May cause problems with impulse control and impulsive behaviors (5.9)
- May cause coronary events (5.10)
- May prolong QTc and cause torsades de pointes or sudden death (5.11)

6 ADVERSE REACTIONS

Most common adverse reactions (incidence at least 10% greater on APOKYN than on placebo) were yawning, drowsiness/somnolence, dyskinesias, dizziness/postural hypotension, rhinorrhea, nausea and/or vomiting, hallucination/confusion, and edema/swelling of extremities (6.1)

To report SUSPECTED ADVERSE REACTIONS, contact MDD US Operations, LLC at 1-877-727-6596 or FDA at 1-800-FDA-1088 or www.fda.gov/medwatch.

7 DRUG INTERACTIONS

- Concomitant use of antihypertensive medications and vasodilators: increased risk for hypotension, myocardial infarction, pneumonia, falls, and injuries (7.2)
- Dopamine antagonists such as neuroleptics or metoclopramide, may diminish the effectiveness of APOKYN (7.4)

8 USE IN SPECIFIC POPULATIONS

- Pregnancy: Based on animal data, may cause fetal harm (8.1)
- Geriatric Use: In clinical trials, patients 65 years of age and older were more likely to experience certain adverse events (8.5)

FULL PRESCRIBING INFORMATION

1 INDICATIONS AND USAGE

APOKYN (apomorphine hydrochloride injection) is indicated for the acute, intermittent treatment of hypomobility, "off" episodes ("end-of-dose wearing off" and unpredictable "on/off" episodes) in patients with advanced Parkinson's disease. APOKYN has been studied as an adjunct to other medications [see Clinical Studies (14)] .

2 DOSAGE AND ADMINISTRATION

2.1 Important Administration Instructions

APOKYN is indicated for subcutaneous administration only [see Warnings and Precautions (5.1)] and only by a multiple-dose APOKYN Pen with supplied cartridges. The initial dose and dose titrations should be performed by a healthcare provider. Blood pressure and pulse should be measured in the supine and standing position before and after dosing.

A caregiver or patient may administer APOKYN if a healthcare provider determines that it is appropriate. Instruct patients to follow the directions provided in the Patients Instructions For Use. Because the APOKYN Pen has markings in milliliters (mL), the prescribed dose of APOKYN should be expressed in mL to avoid confusion.

Visually inspect the APOKYN drug product through the viewing window for particulate matter and discoloration prior to administration. The solution should not be used if discolored (it should be colorless), or cloudy, or if foreign particles are present. Rotate the injection site and use proper aseptic technique [see How Supplied/Storage and Handling (16) and Patient Counseling Information (17)] .

2.2 Premedication and Concomitant Medication

Because of the incidence of nausea and vomiting with APOKYN, it is recommended that treatment with trimethobenzamide 300 mg three times a day be started 3 days prior to the initial dose of APOKYN [see Warnings and Precautions (5.2)] . Alternatively, consider starting APOKYN therapy at 0.1 mL (1 mg) and titrate based upon effectiveness and tolerance.

If trimethobenzamide is used, it should only be continued as long as necessary to control nausea and vomiting, and generally no longer than two months after initiation of treatment with APOKYN, as trimethobenzamide increases the incidence of somnolence, dizziness, and falls in patients treated with APOKYN [see Warnings and Precautions (5.2)] .

Based on reports of profound hypotension and loss of consciousness when apomorphine was administered with ondansetron, the concomitant use of apomorphine with drugs of the 5HT3 antagonist class including antiemetics (for example, ondansetron, granisetron, dolasetron, palonosetron) and alosetron are contraindicated [see Contraindications (4)].

2.3 Dosing Information

The recommended starting dose of APOKYN is 0.1 mL (1 mg) to 0.2 mL (2 mg). Titrate on the basis of effectiveness and tolerance, up to a maximum recommended dose of 0.6 mL (6 mg) [see Clinical Studies (14)] .

There is no evidence from controlled trials that doses greater than 0.6 mL (6 mg) gave an increased effect Reference ID: 5002510 - 3 - and therefore, individual doses above 0.6 mL (6 mg) are not recommended. The average frequency of dosing in the development program was 3 times per day. There is limited experience with single doses greater than 0.6 mL (6 mg), dosing more than 5 times per day and with total daily doses greater than 2 mL (20 mg).

Begin dosing when patients are in an "off" state. The initial test dose should be a 0.1 mL (1 mg) or 0.2 mL (2 mg) test dose in a setting where medical personnel can closely monitor blood pressure and pulse. Both supine and standing blood pressure and pulse should be checked pre-dose and at 20 minutes, 40 minutes, and 60 minutes post-dose (and after 60 minutes, if there is significant hypotension at 60 minutes). Patients who develop clinically significant orthostatic hypotension in response to this test dose of APOKYN should not be considered candidates for treatment with APOKYN.

If the patient tolerates the initial test dose, and responds adequately, the starting dose should be the same as the test dose, used on an as needed basis to treat recurring "off" episodes. If needed, the dose can be increased in 0.1 mL (1 mg) increments every few days on an outpatient basis.

The general principle guiding subsequent dosing (described in detail below) is to determine that the patient needs and can tolerate a higher test dose, 0.3 mL or 0.4 mL (3 mg or 4 mg, respectively) under close medical supervision. A trial of outpatient dosing may follow (periodically assessing both efficacy and tolerability), using a dose 0.1 mL (1 mg) lower than the tolerated test dose.

If the patient tolerates a 0.1 mL (1 mg) test dose but does not respond adequately, a test dose of 0.2 mL (2 mg) may be administered under medical supervision, at least 2 hours after the initial test dose, at the next observed "off" period. If the patient tolerates a 0.2 mL (2 mg) test dose but does not respond adequately, a test dose of 0.4 mL (4 mg) may be administered under medical supervision, at least 2 hours after the initial test dose, at the next observed "off" period. Patients who do not tolerate 0.2 mL (2 mg) may need to be titrated slowly. If the patient tolerates and responds to a test dose of 0.4 mL (4 mg), the initial maintenance dose should be 0.3 mL (3 mg) used on an as needed basis to treat recurring "off" episodes as an outpatient. If needed, the dose can be increased in 0.1 mL (1 mg) increments every few days on an outpatient basis.

If the patient does not tolerate a test dose of 0.4 mL (4 mg), a test dose of 0.3 mL (3 mg) may be administered during a separate "off" period under medical supervision, at least 2 hours after the previous dose. If the patient tolerates the 0.3 mL (3 mg) test dose, the initial maintenance dose should be 0.2 mL (2 mg) used on an as needed basis to treat existing "off" episodes. If needed, and the 0.2 mL (2 mg) dose is tolerated, the dose can be increased to 0.3 mL (3 mg) after a few days. In such a patient, the dose should ordinarily not be increased to 0.4 mL (4 mg) on an outpatient basis.

2.4 Dosing in Patients with Renal Impairment

For patients with mild and moderate renal impairment, the test dose and starting dose should be reduced to 0.1 mL (1 mg) [see Clinical Pharmacology (12.3) and Use in Specific Populations (8.6)] .

2.5 Re-treatment and Interruption in Therapy

If a single dose of APOKYN is ineffective for a particular "off" period, a second dose should not be given for that "off" episode. The efficacy of the safety of administering a second dose for a single "off" episode has not been studied systematically. Do not administer a repeat dose of APOKYN sooner than 2 hours after the last dose.

Patients who have an interruption in therapy of more than a week should be restarted on a 0.2 mL (2 mg) dose and gradually titrated to effect and tolerability.

3 DOSAGE FORMS AND STRENGTHS

APOKYN injection: 30 mg/3 mL (10 mg/mL) apomorphine hydrochloride (as apomorphine hydrochloride hemihydrate), USP as a clear, colorless, sterile, solution in a single-patient-use cartridge for use with a manual reusable pen injector (APOKYN Pen).

4 CONTRAINDICATIONS

APOKYN is contraindicated in patients:

- Using concomitant drugs of the 5HT3 antagonist class including antiemetics (e.g., ondansetron, granisetron, dolasetron, palonosetron) and alosetron [see Drug Interactions (7.1)] . There have been reports of profound hypotension and loss of consciousness when APOKYN was administered with ondansetron.
- With hypersensitivity/allergic reaction to apomorphine or to any of the excipients of APOKYN, including a sulfite (i.e., sodium metabisulfite). Angioedema or anaphylaxis may occur [see Warnings and Precautions (5.13)].

5 WARNINGS AND PRECAUTIONS

5.1 Serious Adverse Reactions After Intravenous Administration

Following intravenous administration of APOKYN, serious adverse reactions including thrombus formation and pulmonary embolism due to intravenous crystallization of apomorphine have occurred. Consequently, APOKYN should not be administered intravenously.

5.2 Nausea and Vomiting

Nausea and vomiting, which may be severe, can happen with APOKYN when it is administered at recommended doses. Because of this, in domestic clinical studies, 98% of all patients were premedicated with trimethobenzamide, an antiemetic, for three days prior to study enrollment, and were then encouraged to continue trimethobenzamide for at least 6 weeks. Even with the use of concomitant trimethobenzamide in clinical studies, 31% and 11% of the APOKYN-treated patients had nausea and vomiting, respectively, and 3% and 2% of the patients discontinued APOKYN due to nausea and vomiting, respectively. Among 522 patients treated, 262 (50%) discontinued trimethobenzamide while continuing APOKYN. The average time to discontinuation of trimethobenzamide was about 2 months (range: 1 day to 33 months). For the 262 patients who discontinued trimethobenzamide, 249 patients continued apomorphine without trimethobenzamide for a duration of follow-up that averaged 1 year (range: 0 years to 3 years).

The effect of trimethobenzamide on reducing nausea and vomiting during treatment with APOKYN was evaluated in a 12-week, placebo-controlled study in 194 patients. The study suggests that trimethobenzamide reduces the incidence of nausea and vomiting during the first 4 weeks of APOKYN treatment (incidence of nausea and vomiting 43% on trimethobenzamide vs. 59% on placebo). However, over the 12-week period, compared with placebo, patients treated with trimethobenzamide had a greater incidence of somnolence (19% for trimethobenzamide vs. 12% for placebo), dizziness (14% for trimethobenzamide vs. 8% for placebo), and falls (8% for trimethobenzamide vs. 1% for placebo). Therefore, the benefit of treatment with trimethobenzamide must be balanced with the risk for those adverse events, and treatment with trimethobenzamide should only be continued as long as necessary to control nausea and vomiting, and generally no longer than two months.

The ability of concomitantly administered antiemetic drugs (other than trimethobenzamide) has not been studied. Antiemetics with anti-dopaminergic actions (e.g., haloperidol, chlorpromazine, promethazine, prochlorperazine, metaclopramide) have the potential to worsen the symptoms in patients with Parkinson's disease and should be avoided.

5.3 Falling Asleep During Activities of Daily Living and Somnolence

There have been reports in the literature of patients treated with APOKYN subcutaneous injections who suddenly fell asleep without prior warning of sleepiness while engaged in activities of daily living. Somnolence is commonly associated with APOKYN, and it is reported that falling asleep while engaged in activities of daily living always occurs in a setting of pre-existing somnolence, even if patients do not give such a history. Somnolence was reported in 35% of patients treated with APOKYN and in none of the patients in the placebo group. Prescribers should reassess patients for drowsiness or sleepiness, especially since some of the events occur well after the start of treatment. Prescribers should also be aware that patients may not acknowledge drowsiness or sleepiness until directly questioned about drowsiness or sleepiness during specific activities.

Before initiating treatment with APOKYN, advise patients of the risk of drowsiness and ask them about factors that could increase the risk with APOKYN, such as concomitant sedating medications and the presence of sleep disorders. If a patient develops significant daytime sleepiness or falls asleep during activities that require active participation (e.g., conversations, eating, etc.), APOKYN should ordinarily be discontinued. If a decision is made to continue APOKYN, patients should be advised not to drive and to avoid other potentially dangerous activities. There is insufficient information to determine whether dose reduction will eliminate episodes of falling asleep while engaged in activities of daily living.

5.4 Syncope / Hypotension / Orthostatic Hypotension

In clinical studies, approximately 2% of APOKYN-treated patients experienced syncope. Dopamine agonists, including APOKYN, may cause orthostatic hypotension at any time but especially during dose escalation. Patients with Parkinson's disease may also have an impaired capacity to respond to an orthostatic challenge. For these reasons, Parkinson's disease patients being treated with dopaminergic agonists ordinarily require careful monitoring for signs and symptoms of orthostatic hypotension, especially during dose escalation, and should be informed of this risk.

Patients undergoing titration of APOKYN showed an increased incidence (from 4% pre-dose to 18% post-dose) of systolic orthostatic hypotension (≥ 20 mm Hg decrease) when evaluated at various times after in-office dosing. A small number of patients developed severe systolic orthostatic hypotension (≥ 30 mm Hg decrease and systolic BP ≤ 90 mm Hg) after subcutaneous apomorphine injection. In clinical trials of APOKYN in patients with advanced Parkinson's disease, 59 of 550 patients (11%) had orthostatic hypotension, hypotension, and/or syncope. These events were considered serious in 4 patients (< 1%) and resulted in withdrawal of APOKYN in 10 patients (2%). These events occurred both with initial dosing and during long-term treatment. Whether or not hypotension contributed to other significant adverse events seen (e.g., falls), is unknown. APOKYN causes dose-related decreases in systolic (SBP) and diastolic blood pressure (DBP) [see Clinical Pharmacology (12.2)] .

In a study of healthy subjects, the hypotensive effect of APOKYN on systolic and diastolic blood pressure was exacerbated by the concomitant use of alcohol or sublingual nitroglycerin (0.4 mg). Patients should avoid alcohol when using APOKYN [see Drug Interactions (7.3)] . Patients taking APOKYN should lie down before and after taking sublingual nitroglycerin. Other vasodilators and antihypertensives may also increase the hypotensive effects of APOKYN. Monitor blood pressure for hypotension and orthostatic hypotension in patients taking APOKYN with concomitant antihypertensive medications or vasodilators [see Drug Interactions (7.2, 7.3)].

5.5 Falls

Patients with Parkinson's disease (PD) are at risk of falling due to underlying postural instability, possible autonomic instability, and syncope caused by the blood pressure lowering effects of the drugs used to treat PD. Subcutaneous APOKYN might increase the risk of falling by simultaneously lowering blood pressure and altering mobility [see Clinical Pharmacology (12.2)] .

In clinical trials, 30% of patients had events that could reasonably be considered falls and about 5% of patients had falls that were considered serious.

5.6 Hallucinations / Psychotic-Like Behavior

In clinical studies, hallucinations were reported by 14% of the APOKYN-treated patients. In one randomized, double-blind, placebo-controlled study, hallucinations or confusion occurred in 10% of patients treated with APOKYN and 0% of patients treated with placebo. Hallucinations resulted in discontinuation of APOKYN in 1% of patients.

Postmarketing reports indicate that patients may experience new or worsening mental status and behavioral changes, which may be severe, including psychotic-like behavior after starting or increasing the dose of APOKYN. Other drugs prescribed to improve the symptoms of Parkinson's disease can have similar effects on thinking and behavior. This abnormal thinking and behavior can consist of one or more of a variety of manifestations, including paranoid ideation, delusions, hallucinations, confusion, disorientation, aggressive behavior, agitation, and delirium.

Patients with a major psychotic disorder should ordinarily not be treated with APOKYN because of the risk of exacerbating psychosis. In addition, certain medications used to treat psychosis may exacerbate the symptoms of Parkinson's disease and may decrease the effectiveness of APOKYN [see Drug Interactions (7.3)] .

5.7 Dyskinesias

APOKYN may cause dyskinesia or exacerbate pre-existing dyskinesia. In clinical studies, dyskinesia or worsening of dyskinesia was reported in 24% of patients. Overall, 2% of APOKYN-treated patients withdrew from studies due to dyskinesias.

5.8 Hemolytic Anemia

Hemolytic anemia requiring hospitalization has been reported with apomorphine treatment in the postmarketing setting. Many of the reported cases included positive direct antiglobulin test (Coombs test), suggesting a potential immune-mediated hemolysis. Severe anemia, angina, and dyspnea have occurred with hemolytic anemia. Some patients were treated with high dose glucocorticoids or blood transfusions. Hemolytic anemia can appear at any time after apomorphine treatment. If a patient develops anemia while taking APOKYN, consider a workup for hemolytic anemia. If hemolytic anemia occurs, consider discontinuing APOKYN treatment.

5.9 Impulse Control/Compulsive Behaviors

Case reports suggest that patients can experience intense urges to gamble, increased sexual urges, intense urges to spend money uncontrollably, and other intense urges and the inability to control these urges while taking one or more of the medications, including APOKYN, that increase central dopaminergic tone and that are generally used for the treatment of Parkinson's disease. In some cases, although not all, these urges were reported to have stopped when the dose was reduced or the medication was discontinued. Because patients may not recognize these behaviors as abnormal, it is important for prescribers to specifically ask patients or their caregivers about the development of new or increased gambling urges, sexual urges, uncontrolled spending or other urges while being treated with APOKYN. Physicians should consider dose reduction or stopping the medication if a patient develops such urges while taking APOKYN.

5.10 Coronary Events

In clinical studies, 4% of patients treated with APOKYN experienced angina, myocardial infarction, cardiac arrest and/or sudden death; some cases of angina and myocardial infarction occurred in close proximity to APOKYN dosing (within 2 hours), while other cases of cardiac arrest and sudden death were observed at times unrelated to dosing. APOKYN has been shown to reduce resting systolic and diastolic blood pressure and may have the potential to exacerbate coronary and cerebral ischemia in patients with known cardiovascular and cerebrovascular disease. If patients develop signs and symptoms of coronary or cerebral ischemia, prescribers should re-evaluate the continued use of APOKYN.

5.11 QTc Prolongation and Potential for Proarrhythymic Effects

There is a dose related prolongation of QTc interval after apomorphine exposure similar to that achieved with therapeutic doses of APOKYN [see Clinical Pharmacology (12.2)] . Doses greater than 6 mg do not provide additional clinical benefit and are not recommended.

Drugs that prolong the QTc interval have been associated with torsades de pointes and sudden death. The relationship of QTc prolongation to torsades de pointes is clearest for larger increases (20 msec and greater), but it is possible that smaller QTc prolongations may also increase risk, or increase it in susceptible individuals, such as those with hypokalemia, hypomagnesemia, bradycardia, concomitant use of other drugs that prolong the QTc interval, or genetic predisposition (e.g., congenital prolongation of the QT interval). Although torsades de pointes has not been observed in association with the use of APOKYN at recommended doses in clinical studies, experience is too limited to rule out an increased risk. Palpitations and syncope may signal the occurrence of an episode of torsades de pointes.

The risks and benefits of APOKYN treatment should be considered prior to initiating treatment with APOKYN in patients with risk factors for prolonged QTc.

5.12 Withdrawal-Emergent Hyperpyrexia and Confusion

A symptom complex resembling neuroleptic malignant syndrome (characterized by elevated temperature, muscular rigidity, altered consciousness, and autonomic instability), with no other obvious etiology, has been reported in association with rapid dose reduction, withdrawal of, or changes in antiparkinsonian therapy.

5.13 Hypersensitivity

Hypersensitivity/allergic reactions characterized by urticaria, rash, pruritus, and/or various manifestations of angioedema may occur because of APOKYN or because of its sulfite excipient. APOKYN contains sodium metabisulfite, a sulfite that may cause allergic-type reactions, including anaphylactic symptoms and life-threatening or less severe asthmatic episodes in certain susceptible people. The overall prevalence of sulfite sensitivity in the general population is unknown and probably low. Sulfite sensitivity is seen more frequently in asthmatic than in nonasthmatic people.

5.14 Fibrotic Complications

Cases of retroperitoneal fibrosis, pulmonary infiltrates, pleural effusion, pleural thickening, and cardiac valvulopathy have been reported in some patients treated with ergot-derived dopaminergic agents. While these complications may resolve when the drug is discontinued, complete resolution does not always occur. Although these adverse reactions are believed to be related to the ergoline structure of these dopamine agonists, whether other, nonergot derived dopamine agonists, such as APOKYN, can cause these reactions is unknown.

5.15 Priapism

APOKYN may cause prolonged painful erections in some patients. In clinical studies, painful erections were reported by 3 of 361 APOKYN-treated men, and one patient withdrew from APOKYN therapy because of priapism. Although no patients in the clinical studies required surgical intervention, severe priapism may require surgical intervention.

5.16 Retinal Pathology in Albino Rats

In a 2-year carcinogenicity study of apomorphine in albino rat, retinal atrophy was detected at all subcutaneous doses tested (up to 0.8 mg/kg/day or 2 mg/kg/day in males or females, respectively; less than the maximum recommended human dose of 20 mg/day on a body surface area [mg/m^2] basis). Retinal atrophy/degeneration has been observed in albino rats treated with other dopamine agonists for prolonged periods (generally during 2-year carcinogenicity studies). Retinal findings were not observed in a 39-week subcutaneous toxicity study of apomorphine in monkey at doses up to 1.5 mg/kg/day, a dose similar to the MRHD on a mg/m^2 basis. The clinical significance of the finding in rat has not been established but cannot be disregarded because disruption of a mechanism that is universally present in vertebrates (e.g., disk shedding) may be involved.

6 ADVERSE REACTIONS

The following serious adverse reactions are discussed in more detail in the Warnings and Precautions section of labeling:

- Serious Adverse Reactions After Intravenous Administration [see Warnings and Precautions (5.1)]
- Nausea and Vomiting [see Warnings and Precautions (5.2)]
- Falling Asleep During Activities of Daily Living and Somnolence [see Warnings and Precautions (5.3)]
- Syncope/Hypotension/Orthostatic Hypotension [see Warnings and Precautions (5.4)]
- Falls [see Warnings and Precautions (5.5)]
- Hallucinations/Psychotic-Like Behavior [see Warnings and Precautions (5.6)]
- Dyskinesias [see Warnings and Precautions (5.7)]
- Hemolytic Anemia [see Warnings and Precautions (5.8)
- Impulse Control/Compulsive Behaviors [see Warnings and Precautions (5.9)]
- Coronary Events [see Warnings and Precautions (5.10)]
- QTc Prolongation and Potential for Proarrhythymic Effects [see Warnings and Precautions (5.11)]
- Withdrawal-Emergent Hyperpyrexia and Confusion [see Warnings and Precautions (5.12)]
- Hypersensitivity [see Warnings and Precautions (5.13)]
- Fibrotic Complications [see Warnings and Precautions (5.14)]
- Priapism [see Warnings and Precautions (5.15)]

6.1 Clinical Trials Experience

Because clinical trials are conducted under widely varying conditions, the incidence of adverse reactions (number of unique patients experiencing an adverse reaction associated with treatment per total number of patients treated) observed in the clinical trials of a drug cannot be directly compared to the incidence of adverse reactions in the clinical trials of another drug and may not reflect the incidence of adverse reactions observed in practice.

In placebo-controlled trials, most patients received only one subcutaneous dose of APOKYN. All patients received concomitant levodopa and 86% received a concomitant dopamine agonist. All patients had some degree of spontaneously occurring periods of hypomobility ("off episodes") at baseline.

The most common adverse reactions (APOKYN incidence at least 10% greater than placebo incidence) observed in a placebo-controlled trial were yawning, drowsiness/somnolence, dyskinesias, dizziness/postural hypotension, rhinorrhea, nausea and/or vomiting, hallucination/confusion, and edema/swelling of extremities.

Table 1 presents the most common adverse reactions reported by APOKYN-naïve Parkinson's disease patients who were enrolled in a randomized placebo-controlled, parallel group trial and who were treated for up to 4 weeks (Study 1) [see Clinical Studies (14)] . Individual APOKYN doses in this trial ranged from 2 mg to 10 mg, and were titrated to achieve tolerability and control of symptoms.

Table 1: Adverse Reactions Occurring in Two or More APOKYN-Treated Patients in Study 1
 | APOKYN (n = 20) | PLACEBO (n = 9)
 | % | %
Yawning | 40 | 0
Dyskinesias | 35 | 11
Drowsiness or Somnolence | 35 | 0
Nausea and/or Vomiting | 30 | 11
Dizziness or Postural Hypotension | 20 | 0
Rhinorrhea | 20 | 0
Chest Pain/Pressure/Angina | 15 | 11
Hallucination or Confusion | 10 | 0
Edema/Swelling of Extremities | 10 | 0

Other Adverse Reactions

Injection Site Reactions

Patients treated with APOKYN subcutaneous injections during clinical studies, 26% of patients had injection site reactions, including bruising (16%), granuloma (4%), and pruritus (2%).

In addition to those in Table 1, the most common adverse reactions in pooled APOKYN trials (occurring in at least 5% of the patients) in descending order were injection site reaction, fall, arthralgia, insomnia, headache, depression, urinary tract infection, anxiety, congestive heart failure, limb pain, back pain, Parkinson's disease aggravated, pneumonia, confusion, sweating increased, dyspnea, fatigue, ecchymosis, constipation, diarrhea, weakness, and dehydration.

6.2 Postmarketing Experience

The following adverse reactions have been identified during post-approval use of APOKYN. Because these reactions are reported voluntarily from a population of uncertain size, it is not always possible to reliably estimate their frequency or establish a causal relationship to drug exposure.

Hematologic and Lymphatic Systems: hemolytic anemia [see Warnings and Precautions (5.8)]

7 DRUG INTERACTIONS

7.1 5HT3 Antagonists

Based on reports of profound hypotension and loss of consciousness when APOKYN was administered with ondansetron, the concomitant use of APOKYN with 5HT3 antagonists including antiemetics (for example, ondansetron, granisetron, dolasetron, palonosetron) and alosetron, is contraindicated.

7.2 Antihypertensive Medications and Vasodilators

In clinical studies, the following adverse events were experienced more commonly in patients receiving concomitant antihypertensive medications or vasodilators (n=94) than in patients not receiving these medications (n=456): hypotension (10% vs 4%) [see Warnings and Precautions (5.4)] , myocardial infarction (3% vs 1%), serious pneumonia (5% vs 3%), serious falls (9% vs 3%), and bone and joint injuries (6% vs 2%). Some of the events may be related to the increased incidence of hypotension in patients receiving concomitant antihypertensive medications or vasodilators [see Warnings and Precautions (5.4, 5.5)] .

Concomitant administration of 0.4 mg sublingual nitroglycerin with APOKYN in healthy subjects causes greater decreases in blood pressure compared to APOKYN alone. When nitroglycerin and APOKYN were concomitantly administered to healthy subjects, the mean largest decrease (the mean of each subject's largest drop in blood pressure measured within the 6-hour period following administration of APOKYN) in supine systolic and diastolic blood pressure (measured over 6 hours) was 9.7 mm Hg and 9.3 mm Hg, respectively [see Clinical Pharmacology (12.3)]. The mean largest decrease in standing systolic and diastolic blood pressure was 14.3 mm Hg and 13.5 mm Hg, respectively. Some individuals experienced very large decreases in standing systolic and diastolic blood pressure, up to a maximum decrease of 65 mm Hg and 43 mm Hg, respectively.

In comparison, the mean largest decrease in supine systolic and diastolic blood pressure when APOKYN was administered alone was 6.1 mm Hg and 7.3 mm Hg, respectively, and in standing systolic and diastolic blood pressure was 6.7 mm Hg and 8.4 mm Hg, respectively.

Patients taking APOKYN should lie down before and after taking sublingual nitroglycerin [see Warnings and Precautions (5.4)].

7.3 Alcohol

Concomitant administration of high dose (0.6 g/kg) or low dose (0.3 g/kg) ethanol with APOKYN in healthy subjects causes greater decreases in blood pressure compared to APOKYN alone.

When high dose ethanol and APOKYN were concomitantly administered to healthy subjects, the mean largest decrease (the mean of each subject's largest drop in blood pressure measured within the 6-hour period following administration of APOKYN) for supine systolic and diastolic blood pressure was 9.1 mm Hg and 10.5 mm Hg, respectively [see Clinical Pharmacology (12.3)]. The mean largest standing systolic and diastolic blood pressure decrease was 11.3 mm Hg and 12.6 mm Hg, respectively. In some individuals, the decrease was as high as 61 mm Hg and 51 mm Hg, respectively, for standing systolic and diastolic blood pressure.

When low dose ethanol and APOKYN were concomitantly administered, the mean largest decrease in supine systolic and diastolic blood pressure was 10.2 mm Hg and 9.9 mm Hg, respectively. The mean largest decrease in standing systolic and diastolic blood pressure was 8.4 mm Hg and 7.1 mm Hg, respectively.

In comparison, the mean largest decrease in supine systolic and diastolic blood pressure when APOKYN was administered alone was 6.1 mm Hg and 7.3 mm Hg, respectively, and in standing systolic and diastolic blood pressure was 6.7 mm Hg 8.4 mm Hg, respectively.

Patients should avoid drinking alcohol after using APOKYN [see Warnings and Precautions (5.4)].

7.4 Dopamine Antagonists

Since APOKYN is a dopamine agonist, it is possible that concomitant use of dopamine antagonists, such as the neuroleptics (phenothiazines, butyrophenones, thioxanthenes) or metoclopramide, may diminish the effectiveness of APOKYN. Patients with major psychotic disorders, treated with neuroleptics, should be treated with dopamine agonists only if the potential benefits outweigh the risks.

7.5 Drugs Prolonging the QT/QTc Interval

Caution should be exercised when prescribing APOKYN concomitantly with drugs that prolong the QT/QTc interval [see Warnings and Precautions (5.11)] .

8 USE IN SPECIFIC POPULATIONS

8.1 Pregnancy

Risk Summary

There are no adequate data on the developmental risk associated with use of APOKYN in pregnant women. In animal reproduction studies, apomorphine had adverse developmental effects in rats (increased neonatal deaths) and rabbits (increased incidence of malformation) when administered during pregnancy at clinically relevant doses. These doses were also associated with maternal toxicity [see Data] . In the U.S. general population, the estimated background risk of major birth defects and miscarriage in clinically recognized pregnancies is 2% to 4% and 15% to 20%, respectively. The background risk of major birth defects and miscarriage for the indicated population is unknown.

Data

Animal Data

No adverse developmental effects were observed when apomorphine (0.3, 1, or 3 mg/kg/day) was administered by subcutaneous injection to pregnant rats throughout organogenesis; the highest dose tested is 1.5 times the maximum recommended human dose (MRHD) of 20 mg/day on a mg/m^2 basis. Administration of apomorphine (0.3, 1, or 3 mg/kg/day) by subcutaneous injection to pregnant rabbits throughout organogenesis resulted in an increased incidence of malformations of the heart and/or great vessels at the mid and high doses; maternal toxicity was observed at the highest dose tested. The no-effect dose for adverse developmental effects is less than the MRHD on a mg/m^2 basis.

Apomorphine (0.3, 1, or 3 mg/kg/day), administered by subcutaneous injection to females throughout gestation and lactation, resulted in increased offspring mortality at the highest dose tested, which was associated with maternal toxicity. There were no effects on developmental parameters or reproductive performance in surviving offspring. The no-effect dose for developmental toxicity (1 mg/kg/day) is less than the MRHD on a mg/m^2 basis.

8.2 Lactation

Risk Summary

There are no data on the presence of apomorphine in human milk, the effects of apomorphine on the breastfed infant, or the effects of apomorphine on milk production. The developmental and health benefits of breastfeeding should be considered along with the mother's clinical need for APOKYN and any potential adverse effects on the breastfed infant from APOKYN or from the underlying maternal condition.

8.4 Pediatric Use

Safety and effectiveness in pediatric patients have not been established.

8.5 Geriatric Use

In the APOKYN clinical development program, there were 239 patients less than age 65 treated with APOKYN and 311 patients who were age 65 or older. Confusion and hallucinations were reported more frequently with patients age 65 and older compared to patients with less than age 65. Serious adverse reactions (life-threatening events or events resulting in hospitalization and/or increased disability) were also more common in patients age 65 and older. Patients age 65 and older were more likely to fall (experiencing bone and joint injuries), have cardiovascular events, develop respiratory disorders, and have gastrointestinal events. Patients age 65 and above were also more likely to discontinue APOKYN treatment as a result of one or more adverse reactions.

8.6 Renal Impairment

The starting APOKYN dose should be reduced in patients with mild or moderate renal impairment because the concentration and exposure (Cmax and AUC) are increased in these patients. Studies in subjects with severe renal impairment have not been conducted [see Dosage and Administration (2.4) and Clinical Pharmacology (12.3)] .

8.7 Hepatic Impairment

Caution should be exercised when administrating APOKYN to patients with mild and moderate hepatic impairment because of the increased Cmax and AUC in these patients. Closely monitor patients with mild and moderate hepatic impairment. Studies of subjects with severe hepatic impairment have not been conducted [see Clinical Pharmacology (12.3)] .

9 DRUG ABUSE AND DEPENDENCE

9.2 Abuse

In premarketing clinical experience, APOKYN did not reveal any tendency for a withdrawal syndrome or any drug-seeking behavior. However, there are rare postmarketing reports of abuse of medications containing APOKYN or levodopa. In general, these reports consist of patients taking increasing doses of medication in order to achieve a euphoric state.

10 OVERDOSAGE

A 62-year-old man accidentally injected 25 mg of APOKYN subcutaneously. After 3 minutes, the patient felt nauseated and lost consciousness for 20 minutes. Afterwards, he was alert with a heart rate 40/minute and a supine blood pressure of 90/50. He recovered completely within an hour.

11 DESCRIPTION

APOKYN (apomorphine hydrochloride injection) contains apomorphine hydrochloride, a non-ergoline dopamine agonist. Apomorphine hydrochloride is chemically designated as 6aβ-Aporphine-10,11-diol hydrochloride hemihydrate with a molecular formula of C17H17NO2 ∙ HCl ∙ ½ H2O. Its structural formula and molecular weight are:

Figure 1: Structural Formula and Molecular Weight of Apomorphine

M.W. 312.79

Apomorphine hydrochloride appears as minute, white or grayish-white glistening crystals or as white powder that is soluble in water at 80°C.

APOKYN is a clear, colorless, sterile solution for subcutaneous injection and is available in 3 mL (30 mg) multi-dose cartridges. Each mL of solution contains 10 mg of apomorphine hydrochloride, USP as apomorphine hydrochloride hemihydrate (equivalent to 8.55 mg apomorphine), 1 mg of sodium metabisulfite, NF and 5 mg of benzyl alcohol, NF (preservative) in water for injection, USP. In addition, each mL of solution may contain sodium hydroxide, NF and/or hydrochloric acid, NF to adjust the pH of the solution.

12 CLINICAL PHARMACOLOGY

12.1 Mechanism of Action

APOKYN is a non-ergoline dopamine agonist with high in vitro binding affinity for the dopamine D4 receptor, and moderate affinity for the dopamine D2, D3, and D5, and adrenergic α1D, α2B, α2C receptors. The precise mechanism of action of APOKYN as a treatment for Parkinson's disease is unknown, although it is believed to be due to stimulation of post-synaptic dopamine D2-type receptors within the caudate-putamen in the brain.

12.2 Pharmacodynamics

Prolongation of the QTc Interval

In a thorough QT study at exposures similar to those achieved with the recommended dosing, apomorphine resulted in a prolongation of QTcF of 10 msec (90% upper confidence interval of 16 msec). The thorough QT study also identified a significant exposure-response relationship between apomorphine concentration and QTcF.

Decreases in Blood Pressure

Dose-dependent mean decreases in systolic blood pressure ranged from 5 mm Hg to 16 mm Hg after administration of APOKYN 2 mg and 10 mg, respectively. Dose-dependent mean decreases in diastolic blood pressure ranged from 3 mm Hg to 8 mm Hg after administration of APOKYN 2 mg and 10 mg, respectively. These changes were observed 20 minutes after dosing, and were maximal between 20 and 40 minutes after dosing. Lesser, but still noteworthy blood pressure decreases persisted up to at least 90 minutes after dosing. Effects on blood pressure are additive when APOKYN is coadministered with nitroglycerin or alcohol [see Drug Interactions (7.3, 7.4)].

12.3 Pharmacokinetics

Absorption

Apomorphine hydrochloride is a lipophilic compound that is rapidly absorbed (time to peak concentration ranges from 10 minutes to 60 minutes) following subcutaneous administration into the abdominal wall. After subcutaneous administration, apomorphine appears to have bioavailability equal to that of an intravenous administration. Apomorphine exhibits linear pharmacokinetics over a dose range of 2 mg to 8 mg following a single subcutaneous injection of APOKYN into the abdominal wall in patients with idiopathic Parkinson's disease.

Distribution

The plasma-to-whole blood apomorphine concentration ratio is equal to one. Mean (range) apparent volume of distribution was 218 L (123 L to 404 L). Maximum concentrations in cerebrospinal fluid (CSF) are less than 10% of maximum plasma concentrations and occur 10 minutes to 20 minutes later.

Metabolism and Elimination

The mean apparent clearance (range) is 223 L/hr (125 L/hr to 401 L/hr) and the mean terminal elimination half-life is about 40 minutes (range about 30 minutes to 60 minutes).

The route of metabolism in humans is not known. Potential routes of metabolism in humans include sulfation, N-demethylation, glucuronidation and oxidation. In vitro, apomorphine undergoes rapid autooxidation.

Specific Populations

The clearance of apomorphine does not appear to be influenced by age, gender, weight, duration of Parkinson's disease, levodopa dose, or duration of therapy.

Renal Impairment

In a study comparing renally-impaired subjects (moderately impaired as determined by estimated creatinine clearance) to healthy matched volunteers, the AUC0-∞ and Cmax values were increased by approximately 16% and 50%, respectively, following a single subcutaneous administration of APOKYN into the abdominal wall. The mean time to peak concentrations and the mean terminal half-life of apomorphine were unaffected by the renal status of the individual. Studies in subjects with severe renal impairment have not been conducted. The starting dose for patients with mild or moderate renal impairment should be reduced [see Dosage and Administration (2.4) and Use in Specific Populations (8.6)] .

Hepatic Impairment

In a study comparing subjects with hepatic impairment (moderately impaired as determined by the Child-Pugh classification method) to healthy matched volunteers, the AUC0-∞ and Cmax values were increased by approximately 10% and 25%, respectively, following a single subcutaneous administration of APOKYN into the abdominal wall. Studies in subjects with severe hepatic impairment have not been conducted [see Dosage and Administration (2.5) and Use in Specific Populations (8.7)] .

Drug Interaction Studies

Carbidopa/levodopa

Levodopa pharmacokinetics were unchanged when subcutaneous APOKYN and levodopa were co-administrated in patients. However, motor response differences were significant. The threshold levodopa concentration necessary for an improved motor response was reduced significantly, leading to an increased duration of effect without a change in the maximal response to levodopa therapy.

Ethanol and Nitroglycerin

Co-administration of low dose ethanol (0.3 g/kg) or nitroglycerin (0.4 mg) with APOKYN in healthy subjects did not have a significant impact on the pharmacokinetics of apomorphine, but high dose ethanol (0.6 g/kg), equivalent to approximately 3 standardized alcohol-containing beverages, increased the Cmax of apomorphine by about 63%. However, the hypotensive effect of APOKYN was increased by the concomitant use of alcohol or of sublingual nitroglycerin [see Warnings and Precautions (5.4) and Drug Interactions (7.2, 7.3)].

Other Drugs Eliminated Via Hepatic Metabolism

Based upon an in vitro study, cytochrome P450 enzymes play a minor role in the metabolism of apomorphine. In vitro studies have also demonstrated that drug interactions are unlikely due to apomorphine acting as a substrate, an inhibitor, or an inducer of cytochrome P450 enzymes.

COMT Interactions

A pharmacokinetic interaction of APOKYN with catechol-O-methyl transferase (COMT) inhibitors or drugs metabolized by this route is unlikely since apomorphine appears not to be metabolized by COMT.

13 NONCLINICAL TOXICOLOGY

13.1 Carcinogenesis, Mutagenesis, Impairment of Fertility

Carcinogenesis

Lifetime carcinogenicity studies of apomorphine were conducted in male (0.1, 0.3, or 0.8 mg/kg/day) and female (0.3, 0.8, or 2 mg/kg/day) rats. Apomorphine was administered by subcutaneous injection for 22 months or 23 months, respectively. In males, there was an increase in Leydig cell tumors at the highest dose tested, which is less than the MRHD (20 mg) on a mg/m^2 basis. This finding is of questionable significance because the endocrine mechanisms believed to be involved in the production of Leydig cell tumors in rats are not relevant to humans. No drug-related tumors were observed in females; the highest dose tested is similar to the MRHD on a mg/m^2 basis.

In a 26-week carcinogenicity study in P53-knockout transgenic mice, there was no evidence of carcinogenic potential when apomorphine was administered by subcutaneous injection at doses up to 20 mg/kg/day (male) or 40 mg/kg/day (female).

Mutagenesis

Apomorphine was mutagenic in the in vitro bacterial reverse mutation (Ames) and the in vitro mouse lymphoma tk assays. Apomorphine was clastogenic in the in vitro chromosomal aberration assay in human lymphocytes and in the in vitro mouse lymphoma tk assay. Apomorphine was negative in the in vivo micronucleus assay in mice.

Impairment of Fertility

Apomorphine was administered subcutaneously at doses up to 3 mg/kg/day (approximately 1.5 times the MRHD on a mg/m^2 basis) to male and female rats prior to and throughout the mating period and continuing in females through gestation day 6. There was no evidence of adverse effects on fertility or on early fetal viability. A significant decrease in testis weight was observed in a 39-week study in cynomolgus monkey at all subcutaneous doses tested (0.3, 1, or 1.5 mg/kg/day); the lowest dose tested is less than the MRHD on a mg/m^2 basis.

In a published fertility study, apomorphine was administered to male rats at subcutaneous doses of 0.2, 0.8, or 2 mg/kg prior to and throughout the mating period. Fertility was reduced at the highest dose tested.

14 CLINICAL STUDIES

The effectiveness of APOKYN in the acute symptomatic treatment of the recurring episodes of hypomobility, "off" episodes ("end-of-dose wearing off" and unpredictable "on/off" episodes), in patients with advanced Parkinson's disease was established in three randomized, controlled trials of APOKYN given subcutaneously (Studies 1, 2, and 3). At baseline in these trials, the mean duration of Parkinson's disease was approximately 11 years. Whereas all patients were using concomitant L-dopa at baseline, 86% of patients were using a concomitant oral dopaminergic agonist, 31% were using a concomitant catechol-ortho-methyl transferase (COMT) inhibitor, and 10% were using a concomitant monoamine B oxidase inhibitor. Study 1 was conducted in patients who did not have prior exposure to APOKYN (i.e., APOKYN naïve) and Studies 2 and 3 were conducted in patients with at least 3 months of APOKYN use immediately prior to study enrollment. Almost all patients without prior exposure to APOKYN began taking an antiemetic (trimethobenzamide) three days prior to starting APOKYN and 50% of patients were able to discontinue the concomitant antiemetic, on average 2 months after initiating APOKYN.

The change from baseline in Part III (Motor Examination) of the Unified Parkinson's Disease Rating Scale (UPDRS) served as the primary outcome assessment measure in each study. Part III of the UPDRS contains 14 items designed to assess the severity of the cardinal motor findings (e.g., tremor, rigidity, bradykinesia, postural instability, etc.) in patients with Parkinson's disease.

Study 1

Study 1 was a randomized, double-blind, placebo-controlled, parallel-group trial in 29 patients with advanced Parkinson's disease who had at least 2 hours of "off" time per day despite an optimized oral regimen for Parkinson's disease including levodopa and an oral dopaminergic agonist. Patients with atypical Parkinson's disease, psychosis, dementia, hypotension, or those taking dopamine antagonists were excluded from participation. In an office setting, hypomobility was allowed to occur by withholding the patients' Parkinson's disease medications overnight. The following morning, patients (in a hypomobile state) were started on study treatment in a 2:1 ratio (2 mg of APOKYN or placebo given subcutaneously). At least 2 hours after the first dose, patients were given additional doses of study medication until they achieved a "therapeutic response" (defined as a response similar to the patient's response to their usual dose of levodopa) or until 10 mg of APOKYN or placebo equivalent was given. At each injection re-dosing, the study drug dose was increased in 2 mg increments up to 4 mg, 6 mg, 8 mg, 10 mg of APOKYN) or placebo equivalent.

Of the 20 patients randomized to APOKYN, 18 achieved a "therapeutic response" at about 20 minutes. The mean APOKYN dose was 5.4 mg (3 patients on 2 mg, 7 patients on 4 mg, 5 patients on 6 mg, 3 patients on 8 mg, and 2 patients on 10 mg). In contrast, of the 9 placebo-treated patients, none reached a "therapeutic response." The mean change from baseline for UPDRS Part III score for APOKYN group (highest dose) was statistically significant compared to that for the placebo group (Table 2).

Table 2: Mean Change from Baseline in UPDRS Motor Score for Intent-to-Treat Population in Study 1
Treatment | Baseline UPDRS Motor Score | Mean Change from Baseline | Difference from placebo
Placebo | 36.3 | - 0.1 | NA
APOKYN | 39.7 | - 23.9 | - 23.8

Study 2

Study 2 used a randomized, placebo-controlled crossover design of 17 patients with Parkinson's disease who had been using APOKYN for at least 3 months. Patients received their usual morning doses of Parkinson's disease medications and were followed until hypomobility occurred, at which time they received either a single dose of subcutaneous APOKYN (at their usual dose) and placebo on different days in random order. UPDRS Part III scores were evaluated over time. The mean dose of APOKYN was 4 mg (2 patients on 2 mg, 9 patients on 3 mg, 2 patients on 4 mg, and 1 patient each on 4.5 mg, 5 mg, 8 mg, and 10 mg). The mean change from baseline UPDRS Part III score for the APOKYN group was statistically significant compared to that for the placebo group (Table 3).

Table 3: Mean Change from Baseline in UPDRS Motor Score for Intent-to-Treat Population in Study 2
Treatment | Baseline UPDRS Motor Score | Mean Change from Baseline | Difference from placebo
Placebo | 40.1 | - 3.0 | NA
APOKYN | 41.3 | - 20.0 | - 17.0

Study 3

Study 3 used a randomized withdrawal design in 4 parallel groups from 62 patients (APOKYN-35; Placebo-27) with Parkinson's disease who had been using APOKYN for at least 3 months. Patients were randomized to one of the following 4 treatments dosed once by subcutaneous administration: APOKYN at the usual dose (mean dose 4.6 mg), placebo at a volume matching the usual APOKYN dose, APOKYN at the usual dose + 2 mg (0.2 mL) (mean dose 5.8 mg), or placebo at a volume matching the usual APOKYN dose + 0.2 mL. Patients received their usual morning doses of Parkinson's disease medications and were followed until hypomobility occurred, at which time they received the randomized treatment. APOKYN doses ranged between 2 mg – 10 mg. The mean change from baseline for the APOKYN group for UPDRS Part III scores at 20 minutes post dosing was statistically significant compared to that for the placebo group (Table 4). Figure 2 describes the mean change from baseline in UPDRS Motor Scores over time for pooled APOKYN and placebo administration.

Table 4: Mean Change from Baseline in UPDRS Motor Score for Intent-to-Treat Population in Study 3
Treatment | Baseline UPDRS Motor Score | Mean Change from Baseline | Difference from placebo
Placebo (Pooled) | 40.6 | - 7.4 | NA
APOKYN (Pooled) | 42.0 | - 24.2 | - 16.8

Figure 2: Mean Change from Baseline in UPDRS Motor Scores of Pooled APOKYN Groups and Placebo Group in Study 3

In Study 3, the mean changes from baseline for UPDRS Part III scores at 20 minutes post dosing for the APOKYN and higher dose APOKYN groups were 24 and 25, respectively. This result suggests that patients chronically treated at a dose of 4 mg might derive little additional benefit from a dose increment of 2 mg. There was also an increased incidence of adverse reactions in patients randomized to higher APOKYN dose.

16 HOW SUPPLIED/STORAGE AND HANDLING

APOKYN injection is supplied as a clear, colorless, sterile solution in cartridges, 30 mg/3 mL (10 mg/mL), for single-patient-use with a pen injector (APOKYN Pen).

NDC 27505-004-05

Cartons of five 3 mL cartridges

APOKYN Pen

The pen injector is provided in a package with five needles and a carrying case.

STORAGE AND HANDLING

Store at 25°C (77°F). Excursions permitted between 15°C to 30°C (59°F to 86°F) [See USP Controlled Room Temperature]

17 PATIENT COUNSELING INFORMATION

Advise the patient to read the FDA-approved patient labeling (Patient Information and Instructions for Use)

Administration with the APOKYN Pen

Instruct patients and caregivers that the APOKYN Pen is dosed in milliliters, not milligrams.

Inform patients and caregivers that it is possible to dial in their usual dose of APOKYN even though the cartridge may contain less than that amount of drug. In this case, they will receive only a partial dose with the injection, and the amount left to inject will appear in the dosing window. To complete the correct dose, patients/caregivers will need to "re-arm" the device and dial in the correct amount of the remaining dose. Patients and caregivers should be alerted to the fact that there may be insufficient drug left in the cartridge to deliver a complete dose (for example, patients and caregivers should be urged to keep records of how many doses they have delivered for each cartridge, so that they can replace any cartridge that has an inadequate amount of drug remaining).

Instruct patients to rotate the injection site and to observe proper aseptic technique.

Advise patients that APOKYN is intended only for subcutaneous injection and must not be given intravenously because of the risk of serious complications such as thrombus formation and pulmonary embolism due to crystallization [see Warnings and Precautions (5.1)].

Hypersensitivity / Allergic Reactions

Advise patients that hypersensitivity/allergic reaction characterized by urticaria, rash, pruritus, and/or various manifestations of angioedema may occur because of APOKYN or any of its excipients including a sulfite (i.e., sodium metabisulfite). Inform patients with a sulfite sensitivity that they may experience various allergic-type reactions, including anaphylactic symptoms and life-threatening asthmatic attacks [see Warnings and Precautions (5.13)]. Advise patients who experience any hypersensitivity/allergic reaction to APOKYN that they should not take APOKYN again [see Contraindications (4)].

Nausea and Vomiting

Advise patients they may experience nausea and/or vomiting, which may be severe, and that treatment with oral trimethobenzamide 300 mg 3 times per day for 3 days prior to starting APOKYN injections has been used to help minimize these symptoms. Alternatively, starting APOKYN at a lower dose and titrating based on individual tolerance and treatment effect may be attempted. Advise patients that APOKYN taken with trimethobenzamide may increase the risks for somnolence, dizziness, and falls, and to consult their healthcare provider before discontinuing trimethobenzamide [see Warnings and Precautions (5.2)] .

Falling Asleep Suddenly and Sedation / Sleepiness

Alert patients to the potential sedating effects of APOKYN, including somnolence and falling asleep while engaged in activities of daily living. Instruct patients not to drive a car or engage in other potentially dangerous activities until they have gained sufficient experience with APOKYN to gauge whether or not it affects their mental and/or motor performance adversely. Advise patients that if increased somnolence or episodes of falling asleep during activities of daily living (e.g., watching television, passenger in a car, etc.) occur, they should not drive or participate in potentially dangerous activities until they have contacted their physician. Because of possible additive effects of alcohol use, advise patients to limit their alcohol intake [see Warnings and Precautions (5.3)].

Hypotension / Orthostatic Hypotension

Advise patients that they may develop postural (orthostatic) hypotension with or without symptoms such as dizziness, nausea, syncope, and sometimes sweating. Hypotension and/or orthostatic symptoms may occur more frequently during initial therapy or with an increase in dose at any time (cases have been seen after months of treatment). Instruct patients to rise slowly after sitting or lying down after taking APOKYN. Inform patients that alcohol and nitroglycerin (and possibly other vasodilators and antihypertensive medications) may potentiate the hypotensive effect of APOKYN [see Warnings and Precautions (5.4)]. Instruct patients ideally to lie down before taking sublingual nitroglycerin and to remain supine and avoid standing for at least 45 minutes after nitroglycerin. Instruct patients taking APOKYN to avoid alcohol while using APOKYN and of the increased hypotensive effects of APOKYN taken with nitroglycerin or by taking APOKYN after alcohol ingestion.

Falls

Alert patients that they may have increased risk for falling when using APOKYN [see Warnings and Precautions (5.5)] .

Hallucinations and/or Psychotic-Like Behavior

Inform patients that hallucinations or other manifestations of psychotic-like behavior can occur. Tell patients if they have a major psychotic disorder, ordinarily they should not use APOKYN because of the risk of exacerbating the psychosis. Patients with a major psychotic disorder should also be aware that many treatments for psychosis may decrease the effectiveness of APOKYN [see Warnings and Precautions (5.6)] .

Dyskinesia

Inform patients that APOKYN may cause and/or exacerbate pre-existing dyskinesias [see Warnings and Precautions (5.7)].

Hemolytic Anemia

Inform patients and caregivers that hemolytic anemia may occur and to contact their healthcare provider if they develop any signs or symptoms [see Warnings and Precautions (5.8)] .

Impulse Control / Compulsive Behaviors

Patients and their caregivers should be alerted to the possibility that they may experience intense urges to spend money uncontrollably, intense urges to gamble, increased sexual urges, binge eating and/or other intense urges and the inability to control these urges while taking APOKYN [see Warnings and Precautions (5.9)] .

Coronary Events

Inform patients that APOKYN may cause coronary events including angina and myocardial infarction and these outcomes could possibly be related to significant hypotension/orthostatic hypotension [see Warnings and Precautions (5.10)].

QTc Prolongation and Potential for Proarrhythymic Effects

Alert patients that APOKYN may cause QTc prolongation and might produce proarrhythmic effects that could cause torsades de pointes and sudden death. Palpitations and syncope may signal the occurrence of an episode of torsades de pointes [see Warnings and Precautions (5.11)].

Withdrawal-Emergent Hyperpyrexia and Confusion

Advise patients to contact their healthcare provider if they wish to discontinue APOKYN or decrease the dose of APOKYN [see Warnings and Precautions (5.12)].

Priapism

Advise patients that APOKYN may cause prolonged painful erections and that if this occurs they should seek medical attention immediately [see Warnings and Precautions (5.15)].

Injection Site Reactions

Inform patients that injections of APOKYN may result in injection site reactions including bruising, granuloma, and pruritus [see Adverse Reactions (6.1)].

Distributed by:

MDD US Operations, LLC, a subsidiary of Supernus Pharmaceuticals, Inc.

9715 Key West Avenue

Rockville, MD 20850

MDD US Operations, LLC is the exclusive licensee and distributor of APOKYN in the United States and Its territories.
© 2022. APOKYN is a registered trademark of BRITUSWIP.
RA-APO_PEN- V18-2022

APOKYN® Pen Instructions for Use

Designed to be used only with
3 mL APOKYN® (apomorphine hydrochloride injection) Cartridges

For more information, call your specialty pharmacy provider or 1-877-7APOKYN (727-6596).

APOKYN®
(apomorphine hydrochloride injection)

APOKYN Pen

- APOKYN® (apomorphine hydrochloride injection) is for under the skin (subcutaneous) injection only.
- Do not inject APOKYN into a vein.
- Do not use the APOKYN® Pen unless you and your care partner have been taught the right way to use it and both of you understand all of the instructions.
- The APOKYN Pen is for use only with 3 mL APOKYN® (apomorphine hydrochloride injection) Cartridges.
- The APOKYN Pen is only for use by 1 patient and should not be shared.

Gray Pen Cap

Gray Pen Body

Pen Needle Unit

Cartridge

a. Clip
Teal Cartridge Holder

b. Black Rod
c. White Dose Window
d. White Dose Knob
e. Teal Injection Button

f. Outer Needle Shield
g. Pink Inner Needle Shield
h. Pen Needle
i. Pink Paper Tab

j. Rubber Septum
k. Metal Cap
l. Cartridge Plunger

Read First: Important Safety Information

- The APOKYN Pen is a medicine delivery device. It is very important that you or your care partner read this Instructions for Use and follow the instructions for using the APOKYN Pen correctly to receive the correct APOKYN dose.
- Always perform a flow check (prime) before every injection and after loading a new cartridge.
- The liquid in the APOKYN Cartridge can cause irritation if it gets on your skin or in your eyes. Flush your eyes with cold water and wash the liquid off your skin right away if this happens.
- The BD pen needle unit is sterile. Avoid contaminating the needle after opening. Do not place it on a surface or touch other items with the needle.
- Do not dial the dose or try to correct a dialing error with the pen needle in the skin. You could receive the wrong dose.
- Be careful when removing the needle. Accidental needle sticks can transmit serious infections.

Never store or carry the APOKYN Pen with a pen needle attached.

Never recap pen with needle attached.

Storing or carrying the APOKYN Pen with a pen needle attached may let:

- Air enter the cartridge
- Medicine leak out

This can affect your APOKYN dose.

The APOKYN Pen should only be used with pen needles (29G × 1/2"). These needles are available through your specialty pharmacy provider or your local pharmacy.

You must use a new, sterile BD pen needle with each injection.

Magnification: 50×

How to Use the APOKYN Pen

Preparing the APOKYN Pen for Cartridge Loading
Step 1. Remove the gray pen cap by pulling it straight off.
Step 2. Unscrew the teal cartridge holder from the gray pen body by turning it clockwise.

Loading a Cartridge
Step 3. Only use APOKYN that is clear and colorless. Do not use an APOKYN Cartridge that contains medicine that is cloudy, green, or contains particles. Call your specialty pharmacy provider for replacement cartridges. Insert the APOKYN Cartridge, metal cap first, into the teal cartridge holder.

Step 4. Lower the gray pen body onto the teal cartridge holder so that the black rod presses against the cartridge plunger. Screw the teal cartridge holder onto the gray pen body. Tighten the pieces by turning the teal cartridge holder clockwise until no gap remains and 1 of the white arrows line up with the white marker on the gray pen body.

Step 5. If you already have a cartridge in the pen and have used the pen, you should check the cartridge through the window in the teal cartridge holder to make sure there is enough APOKYN solution in the cartridge to provide your next dose. If the gray cartridge plunger has reached the red line on the cartridge, remove the cartridge and insert a new cartridge into the pen before attaching the pen needle and preparing the dose.

Attaching the Pen Needle
Step 6. Remove the pink paper tab from the back of a new pen needle. Use a new needle for each injection. Never reuse needles.

Step 7. Holding the APOKYN Pen by the teal cartridge holder, push the pen needle unit onto the pen. Screw the threaded hub of the pen needle onto the teal cartridge holder counter-clockwise. When the needle unit is attached, remove the outer shield that protects the needle with a gentle pull. Save the outer shield. You will use it to remove the needle from the pen after the injection is finished. Do not remove the inner needle shield at this time. The needle is sterile and must stay clean. After opening, do not place the needle on a surface or let it touch anything.

Preparing (Priming) the APOKYN Pen for Use

IMPORTANT – Prior to each injection, it is important that the APOKYN Pen be properly primed.

For a new APOKYN Cartridge (1 that has not been used before), repeat the priming procedure described on the next page (Steps 8-9) 3 or 4 times to make sure all the air has been removed from the needle and cartridge.

For an APOKYN Cartridge you have used before (1 that has been previously primed), repeat the priming procedure described on the next page (Steps 8-9) 1 time to make sure all the air has been removed from the needle and cartridge.

Step 8. You must prepare (prime) the APOKYN Pen for use before injecting the medicine. To prime the APOKYN Pen, set the dose by turning the dose knob to 0.1 mL. This is important so you can get rid of any air bubbles in the cartridge.

Step 9. Remove the inner needle shield. Remember, do not let the needle touch anything. With the needle pointing up, firmly push the injection button in as far as it will go and hold for at least 5 seconds. A small stream of medicine must come out of the end of the needle. If it does not, reset the dose by repeating Step 8. Repeat these steps (Steps 8-9) until a small stream of medicine comes out the end of the needle. When medicine comes out of the end of the needle, the APOKYN Pen is primed for injection and ready to use.
APOKYN medicine can cause staining to fabric and other surfaces it touches. Be careful where you prime the APOKYN Pen.

Setting the Dose
Step 10. To set the dose, turn the white dose knob until the correct dose (number of mLs) is shown in the window. The dose will appear as a red number between two black lines that will line up next to the letters "mL" on the pen body. Make sure the correct number (dose) appears in the window.

Step 11. Dose Correction. If you turn the dose knob past your dose, do not dial backwards. If you dial backwards, APOKYN will be pushed through the needle and you will lose medicine. Continue to turn the dial until it is fully turned. Press the injection button fully. This will reset the dial to zero without pushing medicine out of the needle. Repeat Step 10 to redial your dose.

Giving the Injection
Step 12. APOKYN is only for injection under the skin (subcutaneous injection). Choose an injection site on your stomach area, upper arm or upper leg. Change the site with each injection. Do not inject APOKYN into skin that is red or sore.
Clean the site with an alcohol swab and allow to air dry. Pinch about an inch of skin and fat tissue of your injection site between your thumb and forefinger. With the other hand, insert the needle all the way into the pinched skin.
Step 13. Fully push the teal injection button on the APOKYN Pen. A clicking sound will be heard while the dose is injected. Push the injection button firmly for 5 seconds. Remove the needle from your skin. If medicine keeps dripping from the needle, keep the needle in the skin longer the next time you inject APOKYN.

IMPORTANT – If you set your dose and cannot depress the teal injection button, the cartridge is empty. Remove the pen needle and cartridge and prepare the pen as described in Steps 2-9 with a new cartridge. Set the dose and give the injection.

If you set your dose and the injection button stops before you receive a complete dose, note the number in the window, remove the pen needle and cartridge, and prepare the pen as described in Steps 2-9 with a new cartridge. Set the dose to the number that last appeared in the window and administer the injection. This completes the dose.

Before attempting to replace a cartridge, be sure that a needle unit is not attached to the APOKYN Pen.

Removing the Pen Needle
Step 14. Carefully replace the outer needle shield. Be careful to avoid a needle-stick. Place the outer needle shield in the notch located on the far left side of your carrying case. The opening of the needle shield should be pointing up. Carefully insert the needle (attached to the pen) into the opening of the shield. Without holding onto the shield, push down firmly.

Step 15. Hold the pen by the teal cartridge holder and unscrew the pen needle from the cartridge holder. Recap the pen. Never recap the pen with a needle attached. Safely dispose of used pen needles in a "sharps" container. Your specialty pharmacy provider will provide you with a "sharps" container. Do not throw used needles in a trash can.

Storage Information

–Store APOKYN cartridges at room temperature, 68°F to 77°F (20°C to 25°C)

Excursions permitted between 59 to 86°F (15 to 30°C) [See USP Controlled Room Temperature]

Proper Disposal

- Put your used needles and syringes in an FDA-cleared sharps disposal container right away after use. Do not throw away (dispose of) loose needles and syringes in your household trash.
- If you do not have an FDA-cleared sharps disposal container, you may use a household container that is:
  - made of a heavy-duty plastic
  - able to be closed with a tight-fitting, puncture-resistant lid, without sharps being able to come out
  - upright and stable during use
  - leak-resistant
  - properly labeled to warn of hazardous waste inside the container
- When your sharps disposal container is almost full, you will need to follow your community guidelines for the right way to dispose of your sharps disposal container. There may be state or local laws about how you should throw away used needles and syringes. For more information about safe sharps disposal, and for specific information about sharps disposal in the state that you live in, go to the FDA's website at: http://www.fda.gov/safesharpsdisposal.
- Do not dispose of your used sharps disposal container in your household trash unless your community guidelines permit this. Do not recycle your used sharps disposal container.

Care and Storage

The APOKYN Pen can now be stored in its carrying case. Never store or carry the APOKYN Pen with a pen needle attached.

You must store and care for your pen the right way:

- Avoid exposure to dust, moisture, and cold or hot temperatures.
- Never wash the pen in water or use strong disinfectants. Only a clean, damp cloth should be used for cleaning.
- Do not try to repair the pen if it is damaged or if you cannot solve a problem shown in the following "Troubleshooting" section.
- Do not use pen for more than 1 year after the first use or after the expiration date on the carton.

For more information, call your specialty pharmacy provider or 1-877-7APOKYN (727-6596).

Troubleshooting

PROBLEM | POSSIBLE CAUSE | HOW TO FIX THE PROBLEM
No medicine comes out of the pen (the dosage dial moves freely, but no click is heard). | The pen is in dose correction mode. | Push the injection button all the way in so the dial returns to zero.
The dosage dial does not return to zero during an injection. | The cartridge is empty. | Replace the cartridge as described in Steps 3-5.
The dosage dial does not return to zero during an injection. | The pen needle is clogged. | Replace the pen needle as described in Steps 14 & 6-7.
The dosage dial does not turn easily. | Dust or dirt is on the pen. | Turn the dial past the highest setting on the pen. Wipe all exposed pen surfaces with a clean, damp cloth.
Pen does not close. | Cartridge is inserted incorrectly. | Remove cartridge and reload it. See Steps 3-4.
Injection button will not depress. | Cartridge is empty. | Replace cartridge. See Steps 3-5.
Injection button stops before a complete dose is delivered. | Not enough medication in cartridge to complete the dose. | Replace cartridge. See Steps 3-5.
Pen does not work. | Mechanical failure. | Replace pen. Call your specialty pharmacy provider or 1-877-7APOKYN (727-6596).
Dose numbers and/or white markers wear off. | Repeated use over extended period of time. | Replace pen. Call your specialty pharmacy provider or 1-877-7APOKYN (727-6596).
Too much force needed to depress injection button. | Defective cartridge. | Replace cartridge. See Steps 3-5.
Unable to read the dose numbers through the dose window. | Incorrect cleaning or improper handling. | Replace pen. Call your specialty pharmacy provider or 1-877-7APOKYN (727-6596).
For more information, call your specialty pharmacy provider or 1-877-7APOKYN (727-6596).

Patient Information

APOKYN® (AY-po-kin) (apomorphine hydrochloride injection)

Read this Patient Information before you start using APOKYN and each time you get a refill. There may be new information. This information does not take the place of talking to your healthcare provider about your medical condition or your treatment.

What is APOKYN?

APOKYN is a prescription medicine used to treat acute, intermittent episodes of poor mobility called "off" episodes (end-of-dose wearing "off" or unpredictable "on-off" episodes) in people with advanced Parkinson's disease (PD).

It is not known if APOKYN is safe and effective in children.

Who should not take APOKYN?

Do not take APOKYN if you are:

- taking certain medicines to treat nausea called 5HT3 antagonists including, ondansetron, granisetron, dolasetron, palonosetron, and alosetron. People taking ondansetron together with apomorphine, the active ingredient in APOKYN, have had very low blood pressure and lost consciousness or "blacked out."
- allergic to apomorphine hydrochloride or to any of the ingredients in APOKYN and experience hives, itching, rash, or swelling (e.g., eyes, tongue, etc.). APOKYN also contains a sulfite called sodium metabisulfite. Sulfites can cause severe, life-threatening allergic reactions in some people. An allergy to sulfites is not the same as an allergy to sulfa. People with asthma are more likely to be allergic to sulfites. Call your healthcare provider if you have hives, itching, rash, swelling of the eyes, tongue, lips, chest pain, trouble breathing or swallowing. See the end of this leaflet for a complete list of ingredients in APOKYN.

What should I tell my healthcare provider before taking APOKYN?

Before you start using APOKYN, tell your healthcare provider if you:

- have difficulty staying awake during the daytime
- have dizziness
- have fainting spells
- have low blood pressure
- have asthma
- are allergic to any medicines containing sulfites
- have liver problems
- have kidney problems
- have heart problems
- have had a stroke or other brain problems
- have a mental problem called a major psychotic disorder
- drink alcohol
- are pregnant or plan to become pregnant. It is not known if APOKYN will harm your unborn baby.
- are breastfeeding or plan to breastfeed. It is not known if APOKYN passes into your breast milk. You and your healthcare provider should decide if you will take APOKYN or breastfeed. You should not do both.

Tell your healthcare provider about all the medicines you take, including prescription and non-prescription medicines, vitamins, and herbal supplements.

Using APOKYN with certain other medicines may affect each other. Using APOKYN with other medicines can cause serious side effects.

- If you take nitroglycerin under your tongue while using APOKYN, your blood pressure may decrease and cause dizziness. After taking nitroglycerin, you should lie down and try to continue lying down for at least 45 minutes. You should avoid standing for 45 minutes after taking nitroglycerin.

Know the medicines you take. Keep a list of them to show your healthcare provider or pharmacist when you get a new medicine.

How should I use APOKYN?

- Read the Instructions for Use starting on page 6 of this leaflet for specific information about the right way to use APOKYN.
- Use APOKYN exactly as your healthcare provider tells you to use it.
- Your healthcare provider will tell you how much APOKYN to use and teach you the right way to use it.
- Your healthcare provider may change your dose if needed.
- Do not change your dose of APOKYN or use it more often than prescribed unless your healthcare provider has told you to.
- Do not give another dose of APOKYN sooner than 2 hours after the last dose.
- Your healthcare provider will prescribe APOKYN that comes in prefilled glass cartridges, for single-patient-use, that are used with a special pen injector.
- Your APOKYN pen is dosed in milliliters (mL), not milligrams (mg). Make sure your prescription tells you how many milliliters (mL) to use.
- Inject APOKYN under your skin (subcutaneously). Do not inject APOKYN into a vein.
- Keep a record of how much APOKYN you have used each time you inject or your care partner gives you an injection.
- Use a new needle with each injection. Never reuse a needle.
- APOKYN is a clear and colorless liquid. Do not use APOKYN if it appears cloudy, colored, or to contain particles, and call your pharmacist.
- Your healthcare provider may prescribe another medicine called an antiemetic to take while you are using APOKYN. Antiemetic medicines help to decrease the symptoms of nausea and vomiting that can happen with APOKYN.
- If you take too much APOKYN, call your healthcare provider. If you experience severe or serious side effects such as chest pain or prolonged erection lasting more than 4 hours, go to the nearest hospital emergency room.

What should I avoid while using APOKYN?

- Do not drink alcohol while you are using APOKYN. It can increase your chance of developing serious side effects.
- Do not take medicines that make you sleepy while you are using APOKYN.
- Do not drive, operate machinery, or do other dangerous activities until you know how APOKYN affects you.
- Do not change your body position too fast. Get up slowly from sitting or lying. APOKYN can lower your blood pressure and cause dizziness or fainting.

What are the possible side effects of APOKYN?

APOKYN may cause serious side effects. Call your healthcare provider right away if you have any of the serious side effects, including:

- allergic reaction. An allergic reaction with side effects of hives, itching, rash, swelling (e.g., eyes, tongue, etc.); trouble breathing and/or swallowing may occur after injecting APOKYN.
- blood clots. Injecting APOKYN into a vein (intravenous) can cause blood clots. Do not inject APOKYN in your vein.
- nausea and vomiting. Nausea and vomiting, which may be severe, can happen with APOKYN. Your healthcare provider may prescribe a medicine to help decrease nausea and vomiting. Follow your healthcare providers instructions on how to take and when to stop this medicine.
- sleepiness or falling asleep during the day. Some people treated with APOKYN may get sleepy during the day or fall asleep without warning while doing everyday activities such as talking, eating, or driving a car.
- dizziness. APOKYN can lower your blood pressure and cause dizziness. Dizziness can happen when APOKYN treatment is started or when the APOKYN dose is increased. Do not get up too fast from sitting or after lying down, especially if you have been sitting or lying down for a long period of time.
- falls. The changes that can happen with Parkinson's disease (PD), and the effects of some PD medicines, can increase the risk of falling. APOKYN may also increase your risk of falling.
- hallucinations or psychotic-like behavior. APOKYN can cause or worsen psychotic-like behavior including hallucinations (seeing or hearing things that are not real), confusion, excessive suspicion, aggressive behavior, agitation, delusional beliefs (believing things that are not real), and disorganized thinking.
- sudden uncontrolled movements (dyskinesias). Some people with PD may get sudden, uncontrolled movements after treatment with some PD medicines. APOKYN can cause or make dyskinesias worse.
- low red blood cells (hemolytic anemia). Tell your healthcare provider if you have any of the following signs or symptoms: you become pale, fast heartbeat, feel more tired or weaker than usual, skin or eyes look yellow, chest pain, shortness of breath or trouble breathing, dark-colored urine, fever, dizziness, or confusion.
- intense urges. Some people with PD have reported new or increased gambling urges, increased sexual urges, and other intense urges, while taking PD medicines, including APOKYN.
- heart problems. If you have shortness of breath, fast heartbeat, or chest pain while taking APOKYN, call your healthcare provider or get emergency help right away.
- serious heart rhythm changes (QT prolongation). Tell your healthcare provider right away if you have a change in your heartbeat (a fast or irregular heartbeat), or if you faint.
- injection site problems. Bruising, swelling, and itching can happen at the site where you inject APOKYN.
- fever and confusion. This can happen in some people when their PD medicine is stopped or there is a fast decrease in the dose of their PD medicine.
- tissue changes (fibrotic complications). Some people have had changes in the tissues of their pelvis, lungs, and heart valves when taking medicines called nonergot derived dopamine agonists like APOKYN.
- prolonged painful erections (priaprism). APOKYN may cause prolonged, painful erections in some people. If you have an erection that lasts more than 4 hours you should call your healthcare provider or go to the nearest hospital emergency room right away.
- swelling of ankles/legs. APOKYN may cause swelling, especially in the ankles or legs. Tell your healthcare provider if you notice any swelling.

Other common side effects of APOKYN include:

- yawning
- runny nose
- confusion
- swelling of your hands, arms, legs, and feet

Tell your healthcare provider if you have any side effect that bothers you or that does not go away.

These are not all the possible side effects of APOKYN. For more information, ask your healthcare provider or pharmacist.

Call your doctor for medical advice about side effects. You may report side effects to FDA at 1-800-FDA-1088.

You may also report side effects to US WorldMeds at 1-877-727-6596.

How should I store APOKYN?

- Store APOKYN at room temperature, 68°F to 77°F (20°C to 25°C).
- Safely throw away medicine that is out of date or no longer needed.

Keep APOKYN and all medicines out of the reach of children.

General information about the safe and effective use of APOKYN.

Medicines are sometimes prescribed for purposes other than those listed in a patient information leaflet. Do not use APOKYN for a condition for which it was not prescribed. Do not give APOKYN to other people, even if they have the same symptoms that you have. It may harm them.

This Patient Information leaflet summarizes the most important information about APOKYN. If you would like more information, talk with your healthcare provider. You can ask your pharmacist or healthcare provider for information about APOKYN that is written for health professionals.

For more information, go to www.apokyn.com or call 1-877-727-6596.

What are the ingredients in APOKYN?

Active ingredient: apomorphine hydrochloride, USP

Inactive ingredients: sodium metabisulfite, NF, benzyl alcohol, NF, water for injection, USP. It may also contain sodium hydroxide, NF and/or hydrochloric acid, NF.

This Patient Information and Instructions for Use has been approved by the U.S. Food and Drug Administration.

Distributed by:
MDD US Operations, LLC, as subsidiary of Supernus Pharmaceuticals
Rockville, MD
Revised: 06/2022

MDD US Operations is the exclusive licensee and distributor
of APOKYN in the United States and Its territories.
© 2022. APOKYN is a registered trademark of BRITUSWIP.

INS10001.03

BD Medical Pharmaceutical Systems
1 Becton Drive
Franklin Lakes, NJ 07417, USA

BD and BD Logo are trademarks of Becton, Dickinson and Company.
© 2019. BD

PRINCIPAL DISPLAY PANEL - 30 mg/3 mL Cartridge Carton

NDC 27505-004-05
5 × 3 mL cartridges for single-patient-use

Rx only

APOKYN®
(apomorphine hydrochloride injection)
30 mg/3 mL (10 mg/mL)

For use only with the APOKYN® Pen for
subcutaneous administration.
Not for Intravenous Use.

Single-patient-use with pen injector

CTN10029.01

MDD US Operations, LLC®